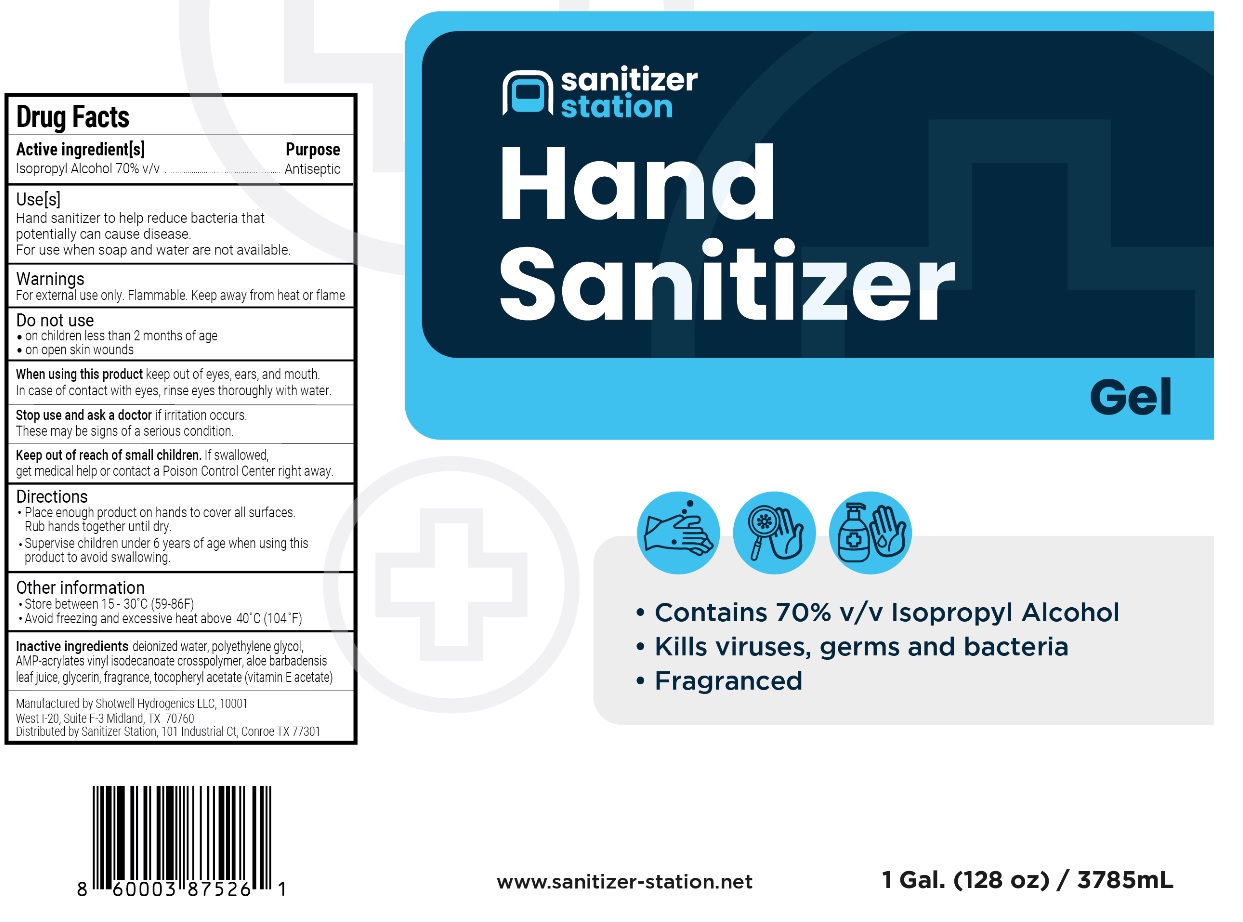 DRUG LABEL: Sanitizer Station Hand Sanitizer
NDC: 82062-101 | Form: GEL
Manufacturer: Pharmore Group LLC DBA Sanitizer Station
Category: otc | Type: HUMAN OTC DRUG LABEL
Date: 20210702

ACTIVE INGREDIENTS: ISOPROPYL ALCOHOL 70 mL/100 mL
INACTIVE INGREDIENTS: WATER; POLYETHYLENE GLYCOL, UNSPECIFIED; ACRYLATES/VINYL ISODECANOATE CROSSPOLYMER (10000 MPA.S NEUTRALIZED AT 0.5%); ALOE VERA LEAF; GLYCERIN; .ALPHA.-TOCOPHEROL ACETATE

Sanitizer Station Hand Sanitizer Gel

Active Ingredient[s]

Isopropyl alcohol 70% v/v

Purpose

Antiseptic

Use[s]

Hand sanitizer to help reduce bacteria that potentially can cause disease.
For use when soap and water are not available.

Warnings

For external use only. Flammable. Keep away from heat or flame.

Do not use
• on children less than 2 months of age
• on open skin wounds

When using this product keep out of eyes, ears, and mouth.
In case of contact with eyes, rinse eyes thoroughly with water.

Stop use and ask doctor if irritation occurs.
These may be signs of a serious condition.

Keep out of reach of children. If swallowed, get medical help or contact a Poison Control Center right away.

Directions

- Place enough product on hands to cover all surfaces.
  Rub hands together until dry.
- Supervise children under 6 years of age when using this product to avoid swallowing.

Other information

• Store between 15-30⁰C (59-86F)
• Avoid freezing and excessive heat above 40⁰C (104⁰F)

Inactive Ingredients

deionized water, polyethylene glycol, AMP-acrylates vinyl isodecanoate crosspolymer, aloe barbadensis leaf juice, glycerin, fragrance, tocopheryl acetate (vitamin E acetate)

- Contains 70% v/v Isopropyl Alcohol
- Kills viruses, germs and bacteria
- Fragranced

www.sanitizer-station.net

Manufactured by Shotwell Hydrogenics LLC, 10001
West l-20, Suite F-3 Midland, TX 70760
Distributed by Sanitizer Station, 101 Industrial Ct, Conroe, TX, 77301